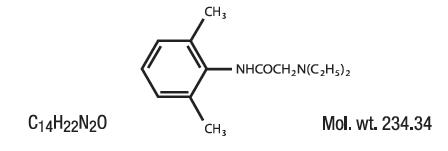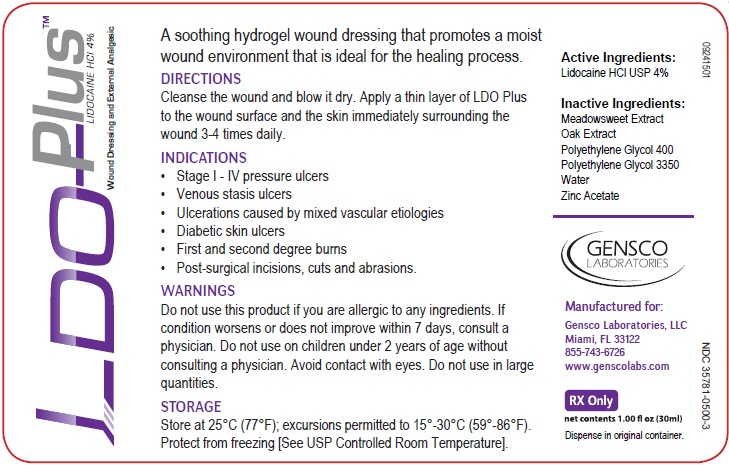 DRUG LABEL: Lidocaine Hydrochloride
NDC: 35781-0500 | Form: GEL
Manufacturer: Gensco Laboratories, LLC
Category: prescription | Type: HUMAN PRESCRIPTION DRUG LABEL
Date: 20151001

ACTIVE INGREDIENTS: LIDOCAINE 40 mg/1 g
INACTIVE INGREDIENTS: FILIPENDULA ULMARIA FLOWER ; QUERCUS ALBA WOOD; POLYETHYLENE GLYCOL 400 ; POLYETHYLENE GLYCOL 3350; WATER; ZINC ACETATE

LDO Plus (Lidocaine HCl USP) 4%

Rx only

DO NOT USE IN THE EYES.

DESCRIPTION

A soothing hydrogel wound dressing that promotes a moist wound environment that is ideal for the healing process

LDO Plus contains Lidocaine HCl USP 4%, which is chemically designated as acetamide, 2-(diethylamino)-N-(2,6-dimethylphenyl)-, and has the following structural formula:

INDICATIONS AND USAGE

- Stage I - IV pressure ulcers
- Venous stasis ulcers
- Ulcerations caused by mixed vascular etiologies
- Diabetic skin ulcers
- First and second degree burns
- Post-surgical incisions, cuts and abrasions.

CONTRAINDICATIONS

LDO Plus contains Lidocaine Hydrochloride USP and is contraindicated in patients with a known history of hypersensitivity to local anesthetics of the amide type or to other components of LDO Plus.

Do not use LDO Plus on traumatized mucosa or in the presence of secondary bacterial infection of the area of proposed application.

WARNINGS

Do not use this product if you are allergic to any ingredients. If condition worsens or does not improve within 7 days, consult a physician. Do not use on children under 2 years of age without consulting a physician.
Avoid contact with eyes. Do not use in large quantities.

For external use only. Not for ophthalmic use.
Keep out of reach of children.

PRECAUTIONS

If irritation or sensitivity occurs or infection appears, discontinue use and institute appropriate therapy. LDO Plus Hydrogel should be used with caution in ill, elderly, debilitated patients and children who may be more sensitive to the systemic effects of Lidocaine Hydrochloride USP. In case of accidental ingestion get medical help or contact poison control center right away.

CARCINOGENESIS, MUTAGENESIS, AND IMPAIRMENT OF FERTILITY

Studies of lidocaine in animals to evaluate the carcinogenic potential of the effect on fertility have not been conducted.

USE IN PREGNANCY

Teratogenic Effects:

Teratogenic Effects. Pregnancy Category B. Reproduction studies have been performed in rats at doses up to 6.6 times the human dose and have revealed no evidence of harm to the fetus caused by Lidocaine Hydrochloride USP. There are, however, no adequate and well-controlled studies in pregnant women. Animal reproduction studies are not always predictive of human response. General consideration should be given to this fact before administering Lidocaine Hydrochloride USP to women of childbearing potential, especially during early pregnancy when maximum organogenesis takes place.

NURSING MOTHERS:

It is not known whether this drug is excreted in human milk. Because many drugs are excreted in human milk, caution should be exercised when Lidocaine Hydrochloride USP. is administered to a nursing woman.

PEDIATRIC USE:

Dosage in children should be reduced, commensurate with age, body weight and physical condition. Caution must be taken to avoid over dosage when applying LDO Plus to large areas of injured or abraded skin, since the systemic absorption of Lidocaine Hydrochloride USP may be increased under such conditions.

ADVERSE REACTIONS:

Adverse experiences following the administration of Lidocaine Hydrochloride USP are similar in nature to those observed with other amide local anesthetic agents. These adverse experiences are, in general, dose-related and may result from high plasma levels caused by excessive dosage or rapid absorption, or may result from a hypersensitivity, idiosyncrasy or diminished tolerance on the part of the patient.
Serious adverse experiences are generally systemic in nature. The following types are those most commonly reported:

Central Nervous System:

CNS manifestations are excitatory and/or depressant and may be characterized by lightheadedness, nervousness, apprehension, euphoria, confusion, dizziness, drowsiness, tinnitus, blurred or double vision, vomiting, sensations of heat, cold or numbness, twitching, tremors, convulsions, unconsciousness, respiratory depression and arrest. The excitatory manifestations may be very brief or may not occur at all, in which case the first manifestation of toxicity may be drowsiness merging into unconsciousness and respiratory arrest. Drowsiness following the administration of lidocaine is usually an early sign of a high blood level of the drug and may occur as a consequence of rapid absorption.

Cardiovascular system

Cardiovascular manifestations are usually depressant and are characterized by bradycardia, hypotension, and cardiovascular collapse, which may lead to cardiac arrest.

Allergic

Allergic reactions are characterized by cutaneous lesions, urticaria, edema or anaphylactoid reactions. Allergic reactions may occur as a result of sensitivity either to the local anesthetic agent or to other components in the formulation. Allergic reactions as a result of sensitivity to lidocaine are extremely rare and, if they occur, should be managed by conventional means. The detection of sensitivity by skin testing is of doubtful value.

DOSAGE AND ADMINISTRATION:

Administration

Cleanse the wound and blow it dry. Apply a thin layer of LDO Plus to the wound surface and the skin immediately surrounding the wound 3-4 times daily.

STORAGE AND HANDLING

Store at 25ºC (77ºF); excursions permitted to 15º-30ºC (59º-86º F). See USP Controlled Room Temperature. Protect from freezing.

HOW SUPPLIED

LDO Plus (Lidocaine HCl USP 4%)

1/2 oz (15g) 15mL Airless Pump - NDC 35781-0500-1
1.00 oz (30g) 30mL Airless Pump - NDC 35781-0500-3
3.00 oz (90g) 90mL Airless Pump - NDC 35781-0500-9

Gensco Labratories, LLC
8550 NW 33rd St Suite 200
Doral, FL 33122